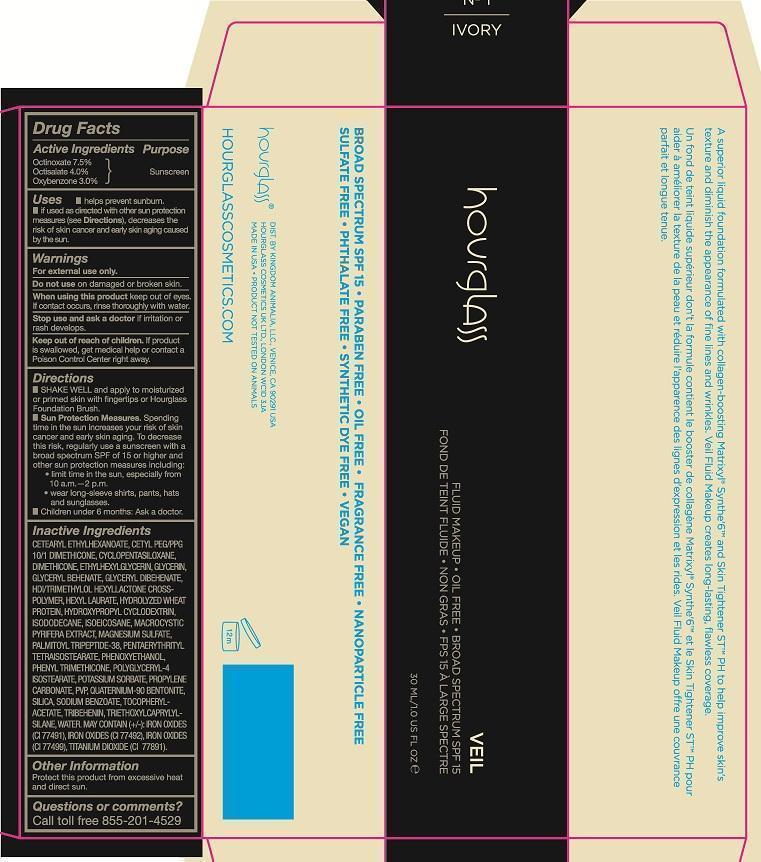 DRUG LABEL: Veil Fluid Makeup Ivory
NDC: 42627-202 | Form: EMULSION
Manufacturer: Kingdom Animalia, LLC. DBA Hourglass Cosmetics
Category: otc | Type: HUMAN OTC DRUG LABEL
Date: 20161205

ACTIVE INGREDIENTS: OCTINOXATE 7.5 g/100 mL; OCTISALATE 4.0 g/100 mL; OXYBENZONE 3.0 g/100 mL
INACTIVE INGREDIENTS: WATER; GLYCERIN; MAGNESIUM SULFATE; PALMITOYL TRIPEPTIDE-5; HYDROLYZED WHEAT PROTEIN (ENZYMATIC, 3000 MW); PHENOXYETHANOL; POTASSIUM SORBATE; BIOTIN; EDETATE TRISODIUM; SODIUM BENZOATE; POLYGLYCERYL-4 ISOSTEARATE; CETYL PEG/PPG-10/1 DIMETHICONE (HLB 5); HEXYL LAURATE; .ALPHA.-TOCOPHEROL ACETATE; GLYCERYL DIBEHENATE; TRIBEHENIN; ETHYLHEXYLGLYCERIN; ISODODECANE; QUATERNIUM-91; PROPYLENE CARBONATE; CYCLOMETHICONE 5 ; DIMETHICONE; CETEARYL ETHYLHEXANOATE; PHENYL TRIMETHICONE; SILICON DIOXIDE; PENTAERYTHRITYL TETRAISOSTEARATE; ISOEICOSANE; TITANIUM DIOXIDE ; FERRIC OXIDE YELLOW; FERRIC OXIDE RED; FERROSOFERRIC OXIDE

Hourglass Veil Fluid Makeup -Ivory

Active Ingredients Purpose
Octinoxate 7.5% Sunscreen
Octisalate 4.0% Sunscreen
Oxybenzone 3.0% Sunscreen

PURPOSE

Enter section text here

Uses

- helps prevent sunburn
- if used as directed with other sun protection measures (see Directions), decrease the risk of skin cancer and early skin aging cause by the sun.

WARNINGS

For external use only.

Do not use on damage or broken skin.

When using this product keep out of eyes. If contact occurs, rinse thoroughly with water.

Stop Use and ask a doctor if irritation or rash develops.

Keep out of reach of children. If product is swallowed, get medical help or contact a Poison Control Center right away.

Directions

- SHAKE WELL, and apply to moisturized or primed skin with fingertips or Hourglass Foundation Brush.
- Sun Protection Measures. Spending time in the sun increases your risk of skin cancer and early skin aging. To decrease this risk, regularly use a sunscreen with a broad spectrum SPF of 15 or higher and other sun protection measures including:
-
  - limit time in the sun, especially from 10 a.m.- 2 p.m.
  - wear long-sleeve shirts, pants, hats and sunglasses.
- Children under 6 months: Ask a doctor.

INACTIVE INGREDIENT

Inactive Ingredients CETEARYL ETHYLHEXANOATE, CETYL PEG/PPG 10/1 DIMETHICONE, CYCLOPENTASILOXANE, DIMETHICONE, ETHYLHEXYLGLYCERIN, GLYCERIN, GLYCERYL BEHENATE, GLYCERYL DIBEHENATE, HDI/TRIMETHYLOL HEXYLLACTONE CROSS-POLYMER, HEXYL LAURATE, HYDROLYZED WHEAT PROTEIN, HYDOXYPROPYL CYCLODEXTRIN, ISODODECANE, ISOEICOSANE, MACROCYSTIC PYRIFERA EXTRACT, MAGNESIUM SULFATE, PALMITOYL TRIPEPTIDE-38, PENTAERYTHRITYL TETRAISOSTEARATE, PHENOXYETHANOL, PHENYL TRIMETHICONE, POLYGLYCERYL-4 ISOSTEARATE, POTASSIUM SORBATE, PROPYLENE CARBONATE, PVP, QUATERNIUM-90 BENTONITE, SILICA, SODIUM BENZOATE, TOCOPHERYL ACETATE, TRIBEHENIN, TRIETHOXYLCAPRYLYLSILANE, WATER. MAY CONTAIN (+/-): IRON OXIDES (CI 77491), IRON OXIDES (CI 77492), IRON OXIDES (CI 77499), TITANIUM DIOXIDE (CI 77891).

Other Information

Protect this product from excessive heat and direct sun.

Questions or comments?

CALL TOLL FREE 855-201-4529

HOW SUPPLIED

DIST. BY KINGDOM ANIMALIA, LLC. VENICE, CA 90291 USA
HOURGLASS COSMETICS, UK LTD, LONDON WC1D 3JA
MADE IN USA PRODUCT NOT TESTED ON ANIMALS